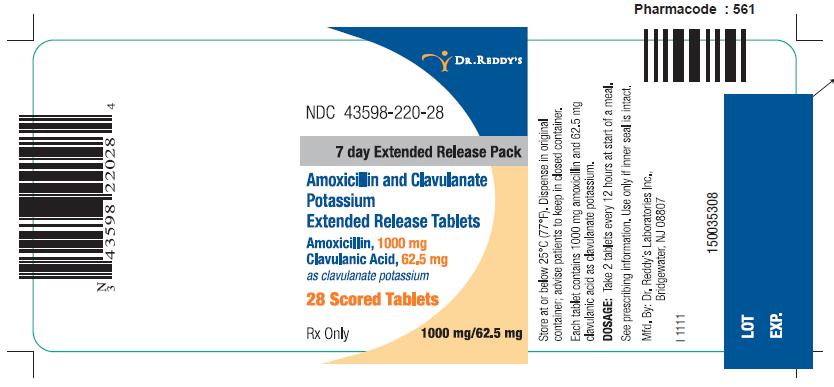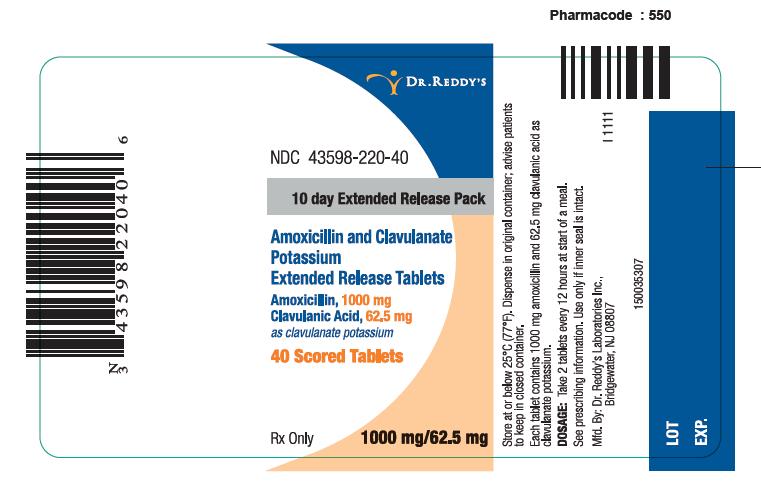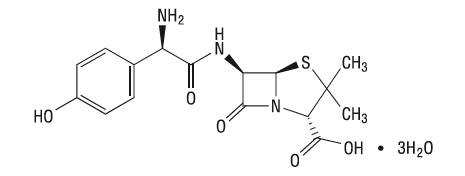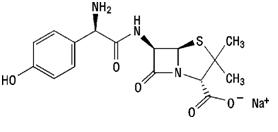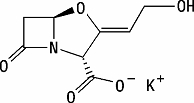 DRUG LABEL: Amoxicillin and Clavulanate Potassium 
NDC: 43598-220 | Form: TABLET, FILM COATED, EXTENDED RELEASE
Manufacturer: Dr. Reddy's Laboratories Inc
Category: prescription | Type: HUMAN PRESCRIPTION DRUG LABEL
Date: 20140117

ACTIVE INGREDIENTS: AMOXICILLIN 562.5 mg/1 1; AMOXICILLIN SODIUM 437.5 mg/1 1; CLAVULANATE POTASSIUM 62.5 mg/1 1
INACTIVE INGREDIENTS: CITRIC ACID MONOHYDRATE; SILICON DIOXIDE; HYPROMELLOSES; MAGNESIUM STEARATE; CELLULOSE, MICROCRYSTALLINE; POLYETHYLENE GLYCOLS; SODIUM STARCH GLYCOLATE TYPE A POTATO; Titanium Dioxide; Xanthan Gum

HIGHLIGHTS OF PRESCRIBING INFORMATION

These highlights do not include all the information needed to use Amoxicillin and Clavulanate Potassium Extended Release Tablets safely and effectively. See full prescribing information for Amoxicillin and Clavulanate Potassium Extended Release Tablets
Amoxicillin and Clavulanate Potassium Extended Release Tablets for oral use.
Initial U.S. Approval:2002
To reduce the development of drug-resistant bacteria and maintain the effectiveness of Amoxicillin and Clavulanate Potassium Extended Release Tablets and other antibacterial drugs, Amoxicillin and Clavulanate Potassium Extended Release Tablets should be used only to treat infections that are proven or strongly suspected to be caused by susceptible bacteria.(1)

1 INDICATIONS AND USAGE

Amoxicillin and Clavulanate Potassium Extended Release Tablets are a combination of a penicillin-class antibacterial drug and a beta-lactamase inhibitor indicated for treatment of community-acquired pneumonia and acute bacterial sinusitis (1).

2 DOSAGE AND ADMINISTRATION

Adults and Pediatric Patients > 40 kg: The recommended dose of Amoxicillin and Clavulanate Potassium Extended Release Tablet is 4,000 mg/250 mg daily at the start of a meal according to the following table (2):

Indication | Dose | Duration
Acute bacterial sinusitis | 2 tablets q12h | 10 days
Community‑acquired pneumonia | 2 tablets q12h | 7-10 days

3 DOSAGE FORMS AND STRENGTHS

Tablets: 1,000 mg of amoxicillin /62.5 mg of clavulanic acid. (3)

4 CONTRAINDICATIONS

History of a serious hypersensitivity reaction (e.g., anaphylaxis or Stevens-Johnson syndrome) to Amoxicillin and Clavulanate Potassium Extended Release Tablet or to other beta-lactams (e.g., penicillins or cephalosporins) (4.1)

History of cholestatic jaundice/hepatic dysfunction associated with Amoxicillin and Clavulanate Potassium Extended Release Tablets. (4.2)

In patients with severe renal impairment (creatinine clearance < 30 mL/min) and in hemodialysis patients. (4.3)

5 WARNINGS AND PRECAUTIONS

Serious (including fatal) hypersensitivity reactions: Discontinue Amoxicillin and Clavulanate Potassium Extended Release Tablets if a reaction occurs. (5.1)

Hepatic dysfunction and cholestatic jaundice: Discontinue if signs/symptoms of hepatitis occur. Monitor liver function tests in patients with hepatic impairment. (5.2)

Clostridium difficile-associated diarrhea (CDAD): Evaluate patients if diarrhea occurs. (5.3)

Patients with mononucleosis who receive Amoxicillin and Clavulanate Potassium Extended Release Tablets develop skin rash. Avoid Amoxicillin and Clavulanate Potassium Extended Release Tablet use in these patients. (5.4)

6 ADVERSE REACTIONS

The most frequently reported adverse reactions were diarrhea (15%), vaginal mycosis (3%) nausea (2%), and loose stools (2%). (6.1)

To report SUSPECTED ADVERSE REACTIONS, contact Dr. Reddy’s Laboratories Inc. at 1-888-375-3784 or FDA at 1-800-FDA-1088 or www.fda.gov/medwatch.

7 DRUG INTERACTIONS

Co-administration with probenecid is not recommended. (7.1)

Concomitant use of Amoxicillin and Clavulanate Potassium Extended Release Tablets and oral anticoagulants may increase the prolongation of prothrombin time. (7.2)

Coadministration with allopurinol increases the risk of rash. (7.3)

Amoxicillin and Clavulanate Potassium Extended Release Tablets may reduce efficacy of oral contraceptives. (7.4)

8 USE IN SPECIFIC POPULATIONS

Renal Impairment: Amoxicillin and Clavulanate Potassium Extended Release Tablet has not been studied in patients with renal impairment. Amoxicillin and Clavulanate Potassium Extended Release Tablet is not recommended for use in patients with severe renal impairment (CrCl < 30 mL/min) or patients on hemodialysis. (2.2, 8.6)

FULL PRESCRIBING INFORMATION

1 INDICATIONS AND USAGE

To reduce the development of drug-resistant bacteria and maintain the effectiveness of Amoxicillin and Clavulanate Potassium Extended Release Tablets and other antibacterial drugs, Amoxicillin and Clavulanate Potassium Extended Release Tablets should be used only to treat infections that are proven or strongly suspected to be caused by susceptible bacteria. When culture and susceptibility information are available, they should be considered in selecting or modifying antibacterial therapy. In the absence of such data, local epidemiology and susceptibility patterns may contribute to the empiric selection of therapy.

Amoxicillin and Clavulanate Potassium Extended Release Tablets is indicated for the treatment of patients with community-acquired pneumonia or acute bacterial sinusitis due to confirmed, or suspected β-lactamase–producing pathogens (i.e., H. influenzae, M. catarrhalis, H. parainfluenzae, K. pneumoniae, or methicillin-susceptible S. aureus) and S. pneumoniae with reduced susceptibility to penicillin (i.e., penicillin MICs = 2 mcg/mL). Amoxicillin and Clavulanate Potassium Extended Release Tablet is not indicated for the treatment of infections due to S. pneumoniae with penicillin MICs ≥ 4 mcg/mL. Data are limited with regard to infections due to S. pneumoniae with penicillin MICs ≥ 4 mcg/ml [see Clinical Studies (14)].

In patients with community-acquired pneumonia in whom penicillin-resistant S. pneumoniae is suspected, bacteriological studies should be performed to determine the causative organisms and their susceptibility when Amoxicillin and Clavulanate Potassium Extended Release Tablet is prescribed.

Acute bacterial sinusitis or community-acquired pneumonia due to a penicillin-susceptible strain of S. pneumoniae plus a β-lactamase–producing pathogen can be treated with another amoxicillin/clavulanate potassium product containing lower daily doses of amoxicillin (i.e., 500 mg every 8 hours or 875 mg every 12 hours). Acute bacterial sinusitis or community-acquired pneumonia due to S. pneumoniae alone can be treated with amoxicillin.

2 DOSAGE AND ADMINISTRATION

Amoxicillin and Clavulanate Potassium Extended Release Tablet should be taken at the start of a meal to enhance the absorption of amoxicillin and to minimize the potential for gastrointestinal intolerance. Amoxicillin and Clavulanate Potassium Extended Release Tablet is not recommended to be taken with a high‑fat meal, because clavulanate absorption is decreased. [see Clinical Pharmacology (12.3)].

2.1 Adults

The recommended dose of Amoxicillin and Clavulanate Potassium Extended Release Tablets is 4,000 mg/250 mg daily according to the following table:

Indication | Dose | Duration
Acute bacterial sinusitis | 2 tablets q12h | 10 days
Community‑acquired pneumonia | 2 tablets q12h | 7-10 days

Tablets of Amoxicillin and Clavulanate Potassium (250 mg or 500 mg) CANNOT be used to provide the same dosages as Amoxicillin and Clavulanate Potassium Extended Release Tablets. This is because Amoxicillin and Clavulanate Potassium Extended Release Tablets contain 62.5 mg of clavulanic acid, while the Amoxicillin and Clavulanate Potassium 250-mg and 500-mg tablets each contain 125 mg of clavulanic acid. In addition, the Extended Release Tablet provides an extended time course of plasma amoxicillin concentrations compared to immediate-release Tablets. Thus, two Amoxicillin and Clavulanate Potassium 500-mg tablets are not equivalent to one Amoxicillin and Clavulanate Potassium Extended Release Tablet.

Scored Amoxicillin and Clavulanate Potassium Extended Release Tablets are available for adult patients who have difficulty swallowing. The scored tablet is not intended to reduce the dosage of medication taken; as stated in the table above, the recommended dose of Amoxicillin and Clavulanate Potassium Extended Release Tablet is two tablets twice a day (every 12 hours).

2.2 Renally Impaired Patients

The pharmacokinetics of Amoxicillin and Clavulanate Potassium Extended Release Tablets have not been studied in patients with renal impairment. Amoxicillin and Clavulanate Potassium Extended Release Tablet is contraindicated in patients with a creatinine clearance of < 30 mL/min and in hemodialysis patients [see Contraindications (4)].

2.3 Hepatically Impaired Patients

Hepatically impaired patients should be dosed with caution and hepatic function monitored at regular intervals [see Warnings and Precautions (5.2)].

2.4 Pediatric Use

Pediatric patients who weigh 40 kg or more and can swallow tablets should receive the adult dose [see Use in Specific Populations (8.4)].

2.5 Geriatric Use

No dosage adjustment is required for the elderly [see Use in Specific Populations (8.5)].

3 DOSAGE FORMS AND STRENGTHS

Amoxicillin and Clavulanate Potassium Extended Release Tablets: Each white, oval film-coated bilayer scored tablet, debossed with AUGMENTIN XR, contains amoxicillin trihydrate and amoxicillin sodium equivalent to a total of 1,000 mg of amoxicillin and clavulanate potassium equivalent to 62.5 mg of clavulanic acid.

4 CONTRAINDICATIONS

4.1 Serious Hypersensitivity Reactions

Amoxicillin and Clavulanate Potassium Extended Release Tablet is contraindicated in patients with a history of serious hypersensitivity reactions (e.g., anaphylaxis or Stevens-Johnson syndrome) to amoxicillin, clavulanate or to other beta-lactam antibacterial drugs (e.g., penicillins and cephalosporins).

4.2 Cholestatic Jaundice/Hepatic Dysfunction

Amoxicillin and Clavulanate Potassium Extended Release Tablet is contraindicated in patients with a previous history of cholestatic jaundice/hepatic dysfunction associated with treatment with amoxicillin/clavulanate potassium.

4.3 Renal Impairment

Amoxicillin and Clavulanate Potassium Extended Release Tablet is contraindicated in patients with severe renal impairment (creatinine clearance < 30 mL/min) and in hemodialysis patients.

5 WARNINGS AND PRECAUTIONS

5.1 Serious Allergic Reactions, Including Anapslaxis

Serious and occasionally fatal hypersensitivity (anaphylactic) reactions have been reported in patients receiving Amoxicillin and Clavulanate Potassium Extended Release Tablets. These reactions are more likely to occur in individuals with a history of penicillin hypersensitivity and/or a history of sensitivity to multiple allergens. Before initiating therapy with Amoxicillin and Clavulanate Potassium Extended Release Tablets, careful inquiry should be made regarding previous hypersensitivity reactions to penicillins, cephalosporins, or other allergens. If an allergic reaction occurs, Amoxicillin and Clavulanate Potassium Extended Release Tablets should be discontinued and appropriate therapy instituted.

5.2 Hepatic Dysfunction

Amoxicillin and Clavulanate Potassium Extended Release Tablets should be used with caution in patients with evidence of hepatic dysfunction. Hepatic toxicity associated with the use of amoxicillin/clavulanate potassium is usually reversible. Deaths have been reported (fewer than 1 death reported per estimated 4 million prescriptions worldwide). These have generally been cases associated with serious underlying diseases or concomitant medications [see Contraindications (4.2) and Adverse Reactions (6.2)].

5.3 Clostridium difficile-Associated Diarrhea

Clostridium difficile associated diarrhea (CDAD) has been reported with use of nearly all antibacterial agents, including Amoxicillin and Clavulanate Potassium Extended Release Tablets, and may range in severity from mild diarrhea to fatal colitis. Treatment with antibacterial agents alters the normal flora of the colon leading to overgrowth of C. difficile.

C. difficile produces toxins A and B which contribute to the development of CDAD. Hypertoxin producing strains of C. difficile cause increased morbidity and mortality, as these infections can be refractory to antimicrobial therapy and may require colectomy. CDAD must be considered in all patients who present with diarrhea following antibiotic use. Careful medical history is necessary since CDAD has been reported to occur over two months after the administration of antibacterial agents.

If CDAD is suspected or confirmed, ongoing antibiotic use not directed against C. difficile may need to be discontinued. Appropriate fluid and electrolyte management, protein supplementation, antibiotic treatment of C. difficile, and surgical evaluation should be instituted as clinically indicated.

5.4 Skin Rash in Patients with Mononucleosis

A high percentage of patients with mononucleosis who receive amoxicillin develop an erythematous skin rash. Thus, Amoxicillin and Clavulanate Potassium Extended Release Tablet should not be administered to patients with mononucleosis.

5.5 Potential for Microbial Overgrowth

The possibility of superinfections with mycotic or bacterial pathogens should be kept in mind during therapy. If superinfections occur (usually involving Pseudomonas spp. or Candida spp.), the drug should be discontinued and/or appropriate therapy instituted.

5.6 Development of Drug-Resistant Bacteria

Prescribing Amoxicillin and Clavulanate Potassium Extended Release Tablet in the absence of a proven or strongly suspected bacterial infection is unlikely to provide benefit to the patient and increases the risk of the development of drug-resistant bacteria.

6 ADVERSE REACTIONS

The following are discussed in more detail in other sections of the labeling:

Anaphylactic reactions [see Warnings and Precautions (5.1)]

Hepatic Dysfunction [see Warnings and Precautions (5.2)]

CDAD [see Warnings and Precautions (5.3)]

6.1 Clinical Trials Experience

Because clinical trials are conducted under widely varying conditions, adverse reaction rates observed in the clinical trials of a drug cannot be directly compared to rates in the clinical trials of another drug and may not reflect the rates observed in practice.

In clinical trials, 5,643 patients have been treated with Amoxicillin and Clavulanate Potassium Extended Release Tablets. The most frequently reported adverse reactions which were suspected or probably drug-related were diarrhea (15%), vaginal mycosis (3%) nausea (2%), and loose stools (2%). Amoxicillin and Clavulanate Potassium Extended Release Tablets had a higher rate of diarrhea which required corrective therapy (4% versus 3% for Amoxicillin and Clavulanate Potassium Extended Release Tablets and all comparators, respectively). Two percent of patients discontinued therapy because of drug-related adverse reactions.

6.2 Postmarketing Experience

In addition to adverse reactions reported from clinical trials, the following have been identified during postmarketing use of Amoxicillin and Clavulanate Potassium products, including Amoxicillin and Clavulanate Potassium Extended Release Tablets. Because they are reported voluntarily from a population of unknown size, estimates of frequency cannot be made. These events have been chosen for inclusion due to a combination of their seriousness, frequency of reporting, or potential causal connection to Amoxicillin and Clavulanate Potassium.

Gastrointestinal: Diarrhea, nausea, vomiting, indigestion, gastritis, stomatitis, glossitis, black “hairy” tongue, mucocutaneous candidiasis, enterocolitis, and hemorrhagic/pseudo membranous colitis. Onset of pseudomembranous colitis symptoms may occur during or after antibiotic treatment.

Hypersensitivity Reactions: Skin rashes, pruritus, urticaria, angioedema, serum sickness-like reactions (urticaria or skin rash accompanied by arthritis, arthralgia, myalgia, and frequently fever), erythema multiforme, Stevens-Johnson syndrome, acute generalized exanthematous pustulosis, hypersensitivity vasculitis, and an occasional case of exfoliative dermatitis (including toxic epidermal necrolysis) have been reported [see Warnings and Precautions (5.1)].

Liver: A moderate rise in AST (SGOT) and/or ALT (SGPT) has been noted in patients treated with ampicillin-class antibiotics, but the significance of these findings is unknown. Hepatic dysfunction, including hepatitis and cholestatic jaundice, [see Contraindications (4)], increases in serum transaminases (AST and/or ALT), serum bilirubin, and/or alkaline phosphatase, has been reported with Amoxicillin and Clavulanate Potassium or Amoxicillin and Clavulanate Potassium Extended Release Tablets. It has been reported more commonly in the elderly, in males, or in patients on prolonged treatment. The histologic findings on liver biopsy have consisted of predominantly cholestatic, hepatocellular, or mixed cholestatic-hepatocellular changes. The onset of signs/symptoms of hepatic dysfunction may occur during or several weeks after therapy has been discontinued. The hepatic dysfunction, which may be severe, is usually reversible. Deaths have been reported [see Contraindications (4.2), Warnings and Precautions (5.2)].

Renal: Interstitial nephritis, hematuria, and crystalluria have been reported [see Overdosage (10)].

Hemic and Lymphatic Systems: Anemia, including hemolytic anemia, thrombocytopenia, thrombocytopenic purpura, eosinophilia, leukopenia, and agranulocytosis have been reported during therapy with penicillins. These reactions are usually reversible on discontinuation of therapy and are believed to be hypersensitivity phenomena. There have been reports of increased prothrombin time in patients receiving Amoxicillin and Clavulanate Potassium and anticoagulant therapy concomitantly.

Central Nervous System: Agitation, anxiety, behavioral changes, confusion, convulsions, dizziness, headache, insomnia, and reversible hyperactivity have been reported rarely.

Miscellaneous: Tooth discoloration (brown, yellow, or gray staining) has been reported. Most reports occurred in pediatric patients. Discoloration was reduced or eliminated with brushing or dental cleaning in most cases.

7 DRUG INTERACTIONS

7.1 Probenecid

Probenecid decreases the renal tubular secretion of amoxicillin. Concurrent use with Amoxicillin and Clavulanate Potassium Extended Release Tablets may result in increased and prolonged blood levels of amoxicillin. Coadministration of probenecid is not recommended.

7.2 Oral Anticoagulants

Abnormal prolongation of prothrombin time (increased international normalized ratio [INR]) has been reported rarely in patients receiving amoxicillin and oral anticoagulants. Appropriate monitoring should be undertaken when anticoagulants are prescribed concurrently. Adjustments in the dose of oral anticoagulants may be necessary to maintain the desired level of anticoagulation.

7.3 Allopurinol

The concurrent administration of allopurinol and amoxicillin substantially increases the incidence of rashes in patients receiving both drugs as compared to patients receiving amoxicillin alone. It is not known whether this potentiation of amoxicillin rashes is due to allopurinol or the hyperuricemia present in these patients. In controlled clinical trials of Amoxicillin and Clavulanate Potassium Extended Release Tablets, 25 patients received concomitant allopurinol and Amoxicillin and Clavulanate Potassium Extended Release Tablets. No rashes were reported in these patients. However, this sample size is too small to allow for any conclusions to be drawn regarding the risk of rashes with concomitant Amoxicillin and Clavulanate Potassium Extended Release Tablets and allopurinol use.

7.4 Oral Contraceptives

Amoxicillin and Clavulanate Potassium Extended Release Tablets may affect intestinal flora, leading to lower estrogen reabsorption and reduced efficacy of combined oral estrogen/progesterone contraceptives.

7.5 Effects on Laboratory Tests

High urine concentrations of amoxicillin may result in false-positive reactions when testing for the presence of glucose in urine using CLINITEST®, Benedict’s Solution, or Fehling’s Solution. Since this effect may also occur with Amoxicillin and Clavulanate Potassium, it is recommended that glucose tests based on enzymatic glucose oxidase reactions be used.

Following administration of amoxicillin to pregnant women, a transient decrease in plasma concentration of total conjugated estriol, estriol-glucuronide, conjugated estrone, and estradiol has been noted.

8 USE IN SPECIFIC POPULATIONS

8.1 Pregnancy

Teratogenic Effects: Pregnancy Category B. Reproduction studies performed in pregnant rats and mice given Amoxicillin and Clavulanate Potassium at oral doses up to 1,200 mg/kg/day revealed no evidence of harm to the fetus due to Amoxicillin and Clavulanate Potassium. In terms of body surface area, the doses in rats were 1.6 times the maximum human oral dose of amoxicillin and 13 times the maximum human dose for clavulanate. For mice, these doses were 0.9 and 7.4 times the maximum human oral dose of Amoxicillin and Clavulanate, respectively. There are, however, no adequate and well controlled studies in pregnant women. Because animal reproduction studies are not always predictive of human response, this drug should be used during pregnancy only if clearly needed.

8.2 Labor and Delivery

Oral ampicillin-class antibiotics are generally poorly absorbed during labor. Studies in guinea pigs have shown that intravenous administration of ampicillin decreased the uterine tone, frequency of contractions, height of contractions, and duration of contractions. However, it is not known whether the use of Amoxicillin and Clavulanate Potassium Extended Release Tablets in humans during labor or delivery has immediate or delayed adverse effects on the fetus, prolongs the duration of labor, or increases the likelihood that forceps delivery or other obstetrical intervention or resuscitation of the newborn will be necessary. In a single study in women with premature rupture of fetal membranes, it was reported that prophylactic treatment with Amoxicillin and Clavulanate Potassium may be associated with an increased risk of necrotizing enterocolitis in neonates.

8.3 Nursing Mothers

Amoxicillin has been shown to be excreted in human milk; therefore, caution should be exercised when Amoxicillin and Clavulanate Potassium Extended Release Tablets is administered to a nursing woman.

8.4 Pediatric Use

The safety and effectiveness of Amoxicillin and Clavulanate Potassium Extended Release Tablets have been established for pediatric patients weighing ≥ 40 kg who are able to swallow tablets. Use of Amoxicillin and Clavulanate Potassium Extended Release Tablets in these pediatric patients is supported by evidence from adequate and well-controlled trials of adults with acute bacterial sinusitis and community-acquired pneumonia with additional data from a pediatric pharmacokinetic study. A pharmacokinetic study in pediatric patients (7 to 15 years of age and weighing ≥ 40 kg) was conducted [see Clinical Pharmacology (12.3)].

The adverse event profile in 44 pediatric patients who received at least one dose of Amoxicillin and Clavulanate Potassium Extended Release Tablet was consistent with the established adverse event profile for the product in adults.

8.5 Geriatric Use

Of the total number of subjects in clinical studies of Amoxicillin and Clavulanate Potassium Extended Release Tablets, 18% were 65 years or older and 7% were 75 years or older. No overall differences in safety and effectiveness were observed between these subjects and younger subjects, and other clinical experience has not reported differences in responses between the elderly and younger patients, but a greater sensitivity of some older individuals cannot be ruled out.

This drug is known to be substantially excreted by the kidney, and the risk of dose dependent toxic reactions to this drug may be greater in patients with impaired renal function. Because elderly patients are more likely to have decreased renal function, it may be useful to monitor renal function.

8.6 Renal Impairment

The pharmacokinetics of Amoxicillin and Clavulanate Potassium Extended Release Tablets have not been studied in patients with renal impairment. Amoxicillin and Clavulanate Potassium Extended Release Tablets is contraindicated in patients with a creatinine clearance of < 30 mL/min and in hemodialysis patients [see Contraindications (4)].

8.7 Hepatic Impairment

Hepatically impaired patients should be dosed with caution and hepatic function monitored at regular intervals [see Contraindications (4.2) and Warnings and Precautions (5.2)].

10 OVERDOSAGE

Following overdosage, patients have experienced primarily gastrointestinal symptoms including stomach and abdominal pain, vomiting, and diarrhea. Rash, hyperactivity, or drowsiness have also been observed in a small number of patients.

In the case of overdosage, discontinue Amoxicillin and Clavulanate Potassium Extended Release Tablets, treat symptomatically, and institute supportive measures as required. If the overdosage is very recent and there is no contraindication, an attempt at emesis or other means of removal of drug from the stomach may be performed. A prospective study of 51 pediatric patients at a poison control center suggested that overdosages of less than 250 mg/kg of amoxicillin are not associated with significant clinical symptoms and do not require gastric emptying^5.

Interstitial nephritis resulting in oliguric renal failure has been reported in a small number of patients after overdosage with amoxicillin.

Crystalluria, in some cases leading to renal failure, has also been reported after amoxicillin overdosage in adult and pediatric patients. In the case of overdosage, adequate fluid intake and diuresis should be maintained to reduce the risk of amoxicillin crystalluria.

Renal impairment appears to be reversible with cessation of drug administration. High blood levels may occur more readily in patients with impaired renal function because of decreased renal clearance of both amoxicillin and clavulanate. Both amoxicillin and clavulanate are removed from the circulation by hemodialysis [see Dosage and Administration (2)].

11 DESCRIPTION

Amoxicillin and Clavulanate Potassium Extended Release Tablet for oral use is an antibacterial combination consisting of the semisynthetic antibacterial amoxicillin (present as amoxicillin trihydrate and amoxicillin sodium) and the β-lactamase inhibitor clavulanate potassium (the potassium salt of clavulanic acid). Amoxicillin is an analog of ampicillin, derived from the basic penicillin nucleus 6‑aminopenicillanic acid. The amoxicillin trihydrate molecular formula is C16H19N3O5S•3H2O, and the molecular weight is 419.45. Chemically, amoxicillin trihydrate is (2S,5R,6R)-6-[(R)-(-)-2-Amino-2-(p-hydroxyphenyl)acetamido]-3,3-dimethyl-7-oxo-4-thia-1-azabicyclo[3.2.0]heptane-2-carboxylic acid trihydrate and may be represented structurally as:

The amoxicillin sodium molecular formula is C16H18N3NaO5S, and the molecular weight is 387.39. Chemically, amoxicillin sodium is [2 -[2α,5α,6β(S*)]]-6-[[Amino(4-hydroxyphenyl)acetyl]amino]-3,3-dimethyl-7-oxo-4-thia-1- azabicyclo[3.2.0]heptane-2-carboxylic acid monosodium salt and may be represented structurally as:

Clavulanic acid is produced by the fermentation of Streptomyces clavuligerus. It is a β-lactam structurally related to the penicillins and possesses the ability to inactivate a wide variety of β-lactamases by blocking the active sites of these enzymes. Clavulanic acid is particularly active against the clinically important plasmid-mediated β-lactamases frequently responsible for transferred drug resistance to penicillins and cephalosporins. The clavulanate potassium molecular formula is C8H8KNO5, and the molecular weight is 237.25. Chemically, clavulanate potassium is potassium (Z)-(2R,5R)-3-(2-hydroxy ethylidene)-7-oxo-4-oxa-1-azabicyclo[3.2.0]-heptane-2-carboxylate, and may be represented structurally as:

Inactive Ingredients: Citric acid, colloidal silicon dioxide, hypromellose, magnesium stearate, microcrystalline cellulose, polyethylene glycol, sodium starch glycolate, titanium dioxide, and xanthan gum.

Each tablet of Amoxicillin and Clavulanate Potassium Extended Release Tablets contains approximately 13 mg of potassium and 30 mg of sodium.

12 CLINICAL PHARMACOLOGY

12.1 Mechanism of Action

Amoxicillin and Clavulanate Potassium Extended Release Tablet is an antibacterial drug. [see Microbiology (12.4)]

12.3 Pharmacokinetics

Amoxicillin and Clavulanate Potassium Extended Release Tablet is an extended-release formulation which provides sustained plasma concentrations of amoxicillin. Amoxicillin systemic exposure achieved with Amoxicillin and Clavulanate Potassium Extended Release Tablets is similar to that produced by the oral administration of equivalent doses of amoxicillin alone.

Absorption: Amoxicillin and Clavulanate potassium are well absorbed from the gastrointestinal tract after oral administration of Amoxicillin and Clavulanate Potassium Extended Release Tablets.

In a study of healthy adult volunteers, the pharmacokinetics of Amoxicillin and Clavulanate Potassium Extended Release Tablets were compared when administered in a fasted state, at the start of a standardized meal (612 kcal, 89.3 g carb, 24.9 g fat, and 14.0 g protein), or 30 minutes after a high‑fat meal. When the systemic exposure to both amoxicillin and clavulanate is taken into consideration, Amoxicillin and Clavulanate Potassium Extended Release Tablets is optimally administered at the start of a standardized meal. Absorption of amoxicillin is decreased in the fasted state. Amoxicillin and Clavulanate Potassium Extended Release Tablet is not recommended to be taken with a high‑fat meal, because clavulanate absorption is decreased. The pharmacokinetics of the components of Amoxicillin and Clavulanate Potassium Extended Release Tablets following administration of two Amoxicillin and Clavulanate Potassium Extended Release Tablets at the start of a standardized meal are presented in Table 1.

Table 1: Mean (SD) Pharmacokinetic Parameter for Amoxicillin and Clavulanate Following Oral Administration of Two Amoxicillin and Clavulanate Potassium Extended Release Tablets (2,000 mg/125 mg) to Healthy Adult Volunteers (n = 55) Fed a Standardized Meal

Parameter (units) | Amoxicillin | Clavulanate
AUC(0‑inf) (mcg•hr/mL) | 71.6 (16.5) | 5.29 (1.55)
Cmax (mcg/mL) | 17.0 (4.0) | 2.05 (0.80)
Tmax (hours)a | 1.50 (1.00 ‑ 6.00) | 1.03 (0.75 ‑ 3.00)
T1/2 (hours) | 1.27 (0.20) | 1.03 (0.17)

a Median (range).

The half-life of amoxicillin after the oral administration of Amoxicillin and Clavulanate Potassium Extended Release Tablets is approximately 1.3 hours, and that of clavulanate is approximately 1.0 hour.

Distribution: Neither component in Amoxicillin and Clavulanate Potassium Extended Release Tablets is highly protein‑bound; clavulanate has been found to be approximately 25% bound to human serum and amoxicillin approximately 18% bound.

Amoxicillin diffuses readily into most body tissues and fluids, with the exception of the brain and spinal fluid. The results of experiments involving the administration of clavulanic acid to animals suggest that this compound, like amoxicillin, is well distributed in body tissues.

Excretion: Clearance of amoxicillin is predominantly renal, with approximately 60% to 80% of the dose being excreted unchanged in urine, whereas clearance of clavulanate has both a renal (30% to 50%) and a non‑renal component.

Drug Interactions

Concurrent administration of probenecid delays amoxicillin excretion but does not delay renal excretion of clavulanate [see Drug Interactions (7.1)].

In a study of adults, the pharmacokinetics of amoxicillin and clavulanate were not affected by administration of an antacid (MAALOX®), either simultaneously with or 2 hours after Amoxicillin and Clavulanate Potassium Extended Release Tablets.

Pediatrics

In a study of pediatric patients with acute bacterial sinusitis, 7 to 15 years of age, and weighing at least 40 kg, the pharmacokinetics of amoxicillin and clavulanate were assessed following administration of Amoxicillin and Clavulanate Potassium Extended Release Tablets 2000 mg/125 mg (as two 1000 mg/62.5 mg tablets) every 12 hours with food (Table 2).

Table 2: Mean (SD) Pharmacokinetic Parameters for Amoxicillin and Clavulanate Following Oral Administration of Two Amoxicillin and Clavulanate Potassium Extended Release Tablets (2,000 mg/125 mg) Every 12 Hours With Food to Pediatric Patients (7 to 15 Years of Age and Weighing ≥ 40kg) With Acute Bacterial Sinusitis

Parameter (units) | Amoxicillin(n=24) | Clavulanate (n=23)
AUC(0‑τ) (mcg•hr/mL) | 57.8 (15.6) | 3.18 (1.37)
Cmax (mcg/mL) | 11.0 (3.34) | 1.17 (0.67)
Tmax (hours)a | 2.0 (1.0 ‑ 5.0) | 2.0 (1.0 ‑ 4.0)
T1/2 (hours) | 3.32 (2.21)b | 0.94 (0.13)c

a Median (range).

b n=18.

c n=17.

12.4 Microbiology

Mechanism of Action

Amoxicillin binds to penicillin-binding proteins within the bacterial cell wall and inhibits bacterial cell wall synthesis.

Clavulanic acid is a β‑lactam, structurally related to penicillin, that may inactivate certain β‑lactamase enzymes.

Mechanism of Resistance

Resistance to penicillins may be mediated by destruction of the beta-lactam ring by a beta-lactamase, altered affinity of penicillin for target, or decreased penetration of the antibiotic to reach the target site. Amoxicillin alone is susceptible to degradation by β‑lactamases, and therefore its spectrum of activity does not include bacteria that produce these enzymes.

Amoxicillin/clavulanic acid has been shown to be active against most isolates of the following bacteria, both in vitro and in clinical infections as described in the INDICATIONS AND USAGE section (1).

Gram-positive bacteria:

Staphylococcus aureus

Streptococcus pneumoniae

Gram-negative bacteria:

Haemophilus influenzae

Haemophilus parainfluenzae

Klebsiella pneumoniae

Moraxella catarrhalis

The following in vitro data are available, but their clinical significance is unknown.

At least 90 percent of the following bacteria exhibit in vitro minimum inhibitory concentrations (MICs) less than or equal to the susceptible breakpoint for amoxicillin/clavulanic acid.^1 However, the safety and effectiveness of amoxicillin/clavulanic acid in treating clinical infections due to these bacteria have not been established in adequate and well‑controlled clinical trials.

Gram-positive bacteria:

Streptococcus pyogenes

Susceptibility Test Methods: When available, the clinical microbiology laboratory should provide cumulative results of in vitro susceptibility test results for antimicrobial drugs used in local hospitals and practice areas to the physician as periodic reports that describe the susceptibility profile of nosocomial and community‑acquired pathogens.

These reports should aid the physician in selecting an antibacterial drug product for treatment.

Dilution Techniques:

Quantitative methods are used to determine antimicrobial minimum inhibitory concentrations (MICs). These MICs provide estimates of the susceptibility of bacteria to antimicrobial compounds. The MICs should be determined using a standardized test method^1,2 (broth and/or agar). The MIC values should be interpreted according to criteria provided in Table 3.

Diffusion Techniques:

Quantitative methods that require measurement of zone diameters also provide reproducible estimates of the susceptibility of bacteria to antimicrobial compounds. The zone size provides an estimate of the susceptibility of bacteria to antimicrobial compounds. The zone size should be determined using a standardized test method.^1,3 This procedure uses paper disks impregnated with 30 mcg amoxicillin/clavulanate potassium (20 mcg amoxicillin plus 10 mcg clavulanate potassium) to test susceptibility of microorganisms to amoxicillin/clavulanate potassium. Disk diffusion interpretive criteria should be interpreted according to criteria provided in Table 3.

Table 3: Susceptibility Interpretive Criteria for Amoxicillin/ Clavulanate Potassium
 | Minimum Inhibitory Concentration (mcg/mL) |  |  | Disk Diffusion (Zone Diameter in mm)
Pathogen | S | I | R | S | I | R
Streptococcus pneumoniae (nonmeningitis isolates) | ≤ 2/1 | 4/2 | ≥ 8/4 | - | - | -
Haemophilus spp. | ≤ 4/2 | - | ≥ 8/4 | ≥ 20 | - | ≤ 19
Klebsiella pneumoni | ≤ 8/4 | 16/8 | ≥ 32/16 | ≥ 18 | 14 to 17 | ≤ 13

S= Susceptible, I=Intermediate, R=Resistant

NOTE: Susceptibility of staphylococci to amoxicillin/clavulanate may be deduced from testing only penicillin and either cefoxitin or oxacillin.

NOTE: Susceptibility of S. pneumoniae by disk diffusion should be determined using a 1mcg oxacillin disk.

NOTE: For nonmeningitis isolates, a penicillin MIC of ≤ 0.06 mcg/ml (or oxacillin zone ≥ 20 mm) can predict susceptibility to amoxicillin/clavulanate.^1

NOTE: Beta‑lactamase–negative, ampicillin‑resistant (BLNAR) H. influenzae isolates should be considered resistant to amoxicillin/clavulanic acid, despite apparent in vitro susceptibility of some BLNAR isolates to these agents. ^1

A report of Susceptible indicates that the antimicrobial is likely to inhibit growth of the pathogen if the antimicrobial compound in the blood reaches the concentrations at the site of infection necessary to inhibit growth of the pathogen. A report of Intermediate indicates that the result should be considered equivocal, and, if the microorganism is not fully susceptible to alternative, clinically feasible drugs, the test should be repeated. This category implies possible clinical applicability in body sites where the drug is physiologically concentrated. This category also provides a buffer zone that prevents small uncontrolled technical factors from causing major discrepancies in interpretation. A report of Resistant indicates that the antimicrobial is not likely to inhibit growth of the pathogen if the antimicrobial compound reaches the concentrations usually achievable at the infection site; other therapy should be selected.

Quality Control:

Standardized susceptibility test procedures require the use of laboratory controls to monitor and ensure the accuracy and precision of supplies and reagents used in the assay, and the techniques of the individuals performing the test.^1,2,3 Standard amoxicillin/clavulanate potassium powder should provide the following range of MIC noted in Table 4. For the disk diffusion technique using the 30 mcg amoxicillin/clavulanate potassium disk, the criteria in Table 4 should be achieved.

Table 4: Acceptable Quality Control Ranges for Susceptibility Testing
Quality Control Organism | Minimum Inhibitory Concentration Range (mcg/mL) | Disk Diffusion Zone Diameters (mm)
Escherichia coli ATCC®abc 35218 | 4/2 to 16/8 | 17 to 22
Escherichia coli ATCC 25922 | 2/1 to 8/4 | 18 to 24
Haemophilus influenzae ATCC 49247 | 2/1 to 16/8 | 15 to 23
Staphylococcus aureus ATCC 29213 | 0.12/0.06 to 0.5/0.25 | -
Staphylococcus aureus ATCC 25923 | - | 28 to 36
Streptococcus pneumoniae ATCC 49619 | 0.03/0.015 to 0.12/0.06 | -

[a ATCC = American Type Culture Collection.] [b QC strain recommended for testing beta-lactam/beta-lactamase inhibitor combinations.c This strain may lose its plasmid and develop susceptibility to beta-lactam antimicrobial agents after repeated transfers onto media. Minimize by removing new culture from storage at least monthly, or whenever the strain begins to show increased zone diameters to ampicillin, piperacillin or ticarcillin.^1]

13 NONCLINICAL TOXICOLOGY

13.1 Carcinogenesis, Mutagenesis, Impairment Of Fertility

Long‑term studies in animals have not been performed to evaluate carcinogenic potential. The mutagenic potential of Amoxicillin and Clavulanate Potassium was investigated in vitro with an Ames test, a human lymphocyte cytogenetic assay, a yeast test, and a mouse lymphoma forward mutation assay, and in vivo with mouse micronucleus tests and a dominant lethal test. All were negative apart from the in vitro mouse lymphoma assay, where weak activity was found at very high, cytotoxic concentrations. Amoxicillin and Clavulanate Potassium at oral doses of up to 1,200 mg/kg/day (1.9 times the maximum human dose of amoxicillin and 15 times the maximum human dose of clavulanate based on body surface area) was found to have no effect on fertility and reproductive performance in rats dosed with a 2:1 ratio formulation of amoxicillin:clavulanate.

14 CLINICAL STUDIES

14.1 Acute Bacterial Sinusitis :

Adults with a diagnosis of acute bacterial sinusitis (ABS) were evaluated in 3 clinical studies. In one study, 363 patients were randomized to receive either Amoxicillin and Clavulanate Potassium Extended Release Tablets 2,000 mg/125 mg orally every 12 hours or levofloxacin 500 mg orally daily for 10 days in a double‑blind, multicenter, prospective trial. These patients were clinically and radiologically evaluated at the test of cure (day 17‑28) visit. The combined clinical and radiological responses were 84% for Amoxicillin and Clavulanate Potassium Extended Release Tablets and 84% for levofloxacin at the test of cure visit in clinically evaluable patients (95% CI for the treatment difference = ‑9.4, 8.3). The clinical response rates at the test of cure were 87% and 89%, respectively.

The other 2 trials were non‑comparative, multicenter studies designed to assess the bacteriological and clinical efficacy of Amoxicillin and Clavulanate Potassium Extended Release Tablets (2,000 mg/125 mg orally every 12 hours for 10 days) in the treatment of 2288 patients with ABS. Evaluation timepoints were the same as in the prior study. Patients underwent maxillary sinus puncture for culture prior to receiving study medication. Patients with acute bacterial sinusitis due to S. pneumoniae with reduced susceptibility to penicillin were accrued through enrollment in these 2 open‑label non‑comparative clinical trials. Microbiologic eradication rates for key pathogens in these studies are shown in Table 5.

Table 5: Clinical Outcome for ABS
Penicillin MICs of S. pneumoniae Isolates | Intent-To-Treat |  |  | Clinically Evaluable
 | n/Na | % | 95% CIb | n/Na | % | 95% CIb
All S. pneumonia | 344/370 | 93 | — | 318/326 | 98 | —
MIC ≥ 2.0 mcg/mL [c] | 35/36 | 97 | 85.5, 99.9 | 30/31 | 96 | 83.3, 99.9
MIC = 2.0 mcg/mL | 23/24 | 96 | 78.9, 99.9 | 19/20 | 95 | 75.1, 99.9
MIC ≥ 4.0 mcg/mLd | 12/12 | 100 | 73.5, 100 | 11/11 | 100 | 71.5, 100
H. influenza | 265/305 | 87 | — | 242/259 | 93 | —
M. catarrhalis | 94/105 | 90 | — | 86/90 | 96 | —

[a n/N = patients with pathogen eradicated or presumed eradicated/total number of patients.] [b Confidence limits calculated using exact probabilities.c S. pneumoniae strains with penicillin MICs of ≥ 2 mcg/mL are considered resistant to penicillin.d Includes one patient each with S. pneumoniae penicillin MICs of 8 and 16 mcg/mL.]

14.2 Community-Acquired Pneumonia

Four randomized, controlled, double‑blind clinical studies and one non‑comparative study were conducted in adults with community-acquired pneumonia (CAP). In comparative studies, 904 patients received Amoxicillin and Clavulanate Potassium Extended Release Tablets at a dose of 2,000 mg/125 mg orally every 12 hours for 7 or 10 days. In the non‑comparative study to assess both clinical and bacteriological efficacy, 1,122 patients received Amoxicillin and Clavulanate Potassium Extended Release Tablets 2,000 mg/125 mg orally every 12 hours for 7 days. In the 4 comparative studies, the combined clinical success rate at test of cure ranged from 86% to 95% in clinically evaluable patients who received Amoxicillin and Clavulanate Potassium Extended Release Tablets.

Data on the efficacy of Amoxicillin and Clavulanate Potassium Extended Release Tablets in the treatment of community‑acquired pneumonia due to S. pneumoniae with reduced susceptibility to penicillin were accrued from the 4 controlled clinical studies and the 1 non‑comparative study. The majority of these cases were accrued from the non‑comparative study. Results are shown in Table 6.

Table 6: Clinical Outcome for CAP due to S. pneumoniae
Penicillin MICs of S. pneumonia Isolates | Intent-To-Treat |  |  | Clinically Evaluable
 | n/Na | % | 95% CIb | n/Na | % | 95% CIb
All S. pneumonia | 318/367 | 87 | — | 275/297 | 93 | —
MIC ≥ 2.0 mcg/mL [c] | 30/35 | 86 | 69.7, 95.2 | 24/25 | 96 | 79.6, 99.9
MIC = 2.0 mcg/mL | 22/24 | 92 | 73.0, 99.0 | 18/18 | 100 | 81.5, 100
MIC ≥ 4.0 mcg/mLd | 8/11 | 73 | 39.0, 94.0 | 6/7 | 86 | 42.1, 99.6

[a n/N = patients with pathogen eradicated or presumed eradicated/total number of patients.b Confidence limits calculated using exact probabilities.c S. pneumoniae strains with penicillin MICs of ≥ 2 mcg/mL are considered resistant to penicillin.d Includes one patient each with S. pneumoniae penicillin MICs of 8 and 16 mcg/mL in the Intent‑To‑Treat group only.]

15 REFERENCES

1. Clinical and Laboratory Standards Institute (CLSI). Performance Standards for Antimicrobial Susceptibility Testing; Twenty-third Informational Supplement, CLSI document M100-S23. CLSI document M100-S23, Clinical and Laboratory Standards Institute, 950 West Valley Road, Suite 2500, Wayne, Pennsylvania 19087, USA, 2013.

2. Clinical and Laboratory Standards Institute (CLSI). Methods for Dilution Antimicrobial Susceptibility Tests for Bacteria That Grow Aerobically; Approved Standard ‑ Ninth Edition. CLSI Document M7‑A9 Clinical and Laboratory Standards Institute, 940 West Valley Road, Suite 2500, Wayne, Pennsylvania 19087, USA, 2012.

3. Clinical and Laboratory Standards Institute (CLSI). Performance Standards for Antimicrobial Disk Susceptibility Tests; Approved Standard ‑ Eleventh Edition. CLSI Document M2‑A11. Clinical and Laboratory Standards Institute, 940 West Valley Road, Suite 2500, Wayne, Pennsylvania 19087, USA, 2012.

16 HOW SUPPLIED/STORAGE AND HANDLING

Amoxicillin and Clavulanate Potassium Extended Release Tablets: Each white, oval film‑coated bilayer scored tablet, debossed with AUGMENTIN XR, contains amoxicillin trihydrate and amoxicillin sodium equivalent to a total of 1,000 mg of amoxicillin and clavulanate potassium equivalent to 62.5 mg of clavulanic acid.

NDC 43598‑220‑28 Bottles of 28 (7 day Extended Release pack)

NDC 43598‑220‑40 Bottles of 40 (10 day Extended Release pack)

Storage

Dispense in original container

Store tablets at or below 25°C (77°F).

Keep out of reach of children.

17 PATIENT COUNSELING INFORMATION

Advise the patient to read the FDA-approved patient labeling (Patient Information).

17.1 Information for Patients

Counsel patients to take Amoxicillin and Clavulanate Potassium Extended Release Tablets every 12 hours with a low fat meal or snack to reduce the possibility of gastrointestinal upset. If diarrhea develops and is severe or lasts more than 2 or 3 days, call your doctor.

Patients should be counseled that antibacterial drugs, including Amoxicillin and Clavulanate Potassium Extended Release Tablets, should only be used to treat bacterial infections. They do not treat viral infections (e.g., the common cold). When Amoxicillin and Clavulanate Potassium Extended Release Tablet is prescribed to treat a bacterial infection, patients should be told that although it is common to feel better early in the course of therapy, the medication should be taken exactly as directed. Skipping doses or not completing the full course of therapy may: (1) decrease the effectiveness of the immediate treatment, and (2) increase the likelihood that bacteria will develop resistance and will not be treatable by Amoxicillin and Clavulanate Potassium Extended Release Tablets or other antibacterial drugs in the future.

Counsel patients that diarrhea is a common problem caused by antibacterials, and it usually ends when the antibacterial is discontinued. Sometimes after starting treatment with antibacterials, patients can develop watery and bloody stools (with or without stomach cramps and fever) even as late as 2 or more months after having taken their last dose of the antibacterial. If diarrhea is severe or lasts more than 2 or 3 days, patients should contact their physician. Discard any unused medicine.

Patients should be aware that Amoxicillin and Clavulanate Potassium Tablets contain a penicillin class drug product that can cause allergic reactions in some individuals.

AUGMENTIN XR and AUGMENTIN are registered trademarks of GlaxoSmithKline and are licensed to Dr. Reddy's Laboratories, Inc.

MAALOX is a registered trademark of Novartis Consumer Health, Inc.

CLINITEST is a registered trademark of Miles, Inc.

Manufactured by:

Dr. Reddy's Laboratories Tennessee LLC,

Bristol, TN 37620

PACKAGE LABEL PRINCIPAL DISPLAY PANEL SECTION

Principal Display Panel

NDC 43598-220-28

7 day Extended Release Pack

Amoxicillin and Clavulanate Potassium

Extended Release Tablets

Amoxicillin, 1000 MG

Clavulanic Acid, 62.5 MG,

as clavulanate potassium

28 Scored Tablets

Rx only

1000mg/62.5 mg

Store at or below 25oC (77oF).

Dispense in original container; advise patients to keep in closed container.

Each tablet contains 1000 mg amoxicillin and 62.5 mg clavulanic acid as clavulanate potassium.

Dosage: Take 2 tablets every 12 hours at start of a meal.

See prescribing information.Use only if inner seal is intact.

Mfd. By: Dr. Reddy's Laboratories Tennessee LLC.

Bristol, TN 37620

I0513

150035308

PACKAGE LABEL PRINCIPAL DISPLAY PANEL SECTION

Principal Display Panel

NDC 43598-220-40

10 day Extended Release Pack

Amoxicillin and Clavulanate Potassium

Extended Release Tablets

Amoxicillin, 1000 MG

Clavulanic Acid, 62.5 MG,

as clavulanate potassium

40 Scored Tablets

Rx only

1000mg/62.5 mg

Store at or below 25oC (77oF).

Dispense in original container; advise patients to keep in closed container.

Each tablet contains 1000 mg amoxicillin and 62.5 mg clavulanic acid as clavulanate potassium.

Dosage: Take 2 tablets every 12 hours at start of a meal.

See prescribing information.Use only if inner seal is intact.

Mfd. By: Dr. Reddy's Laboratories Tennessee LLC.

Bristol, TN 37620

I0513

150035307